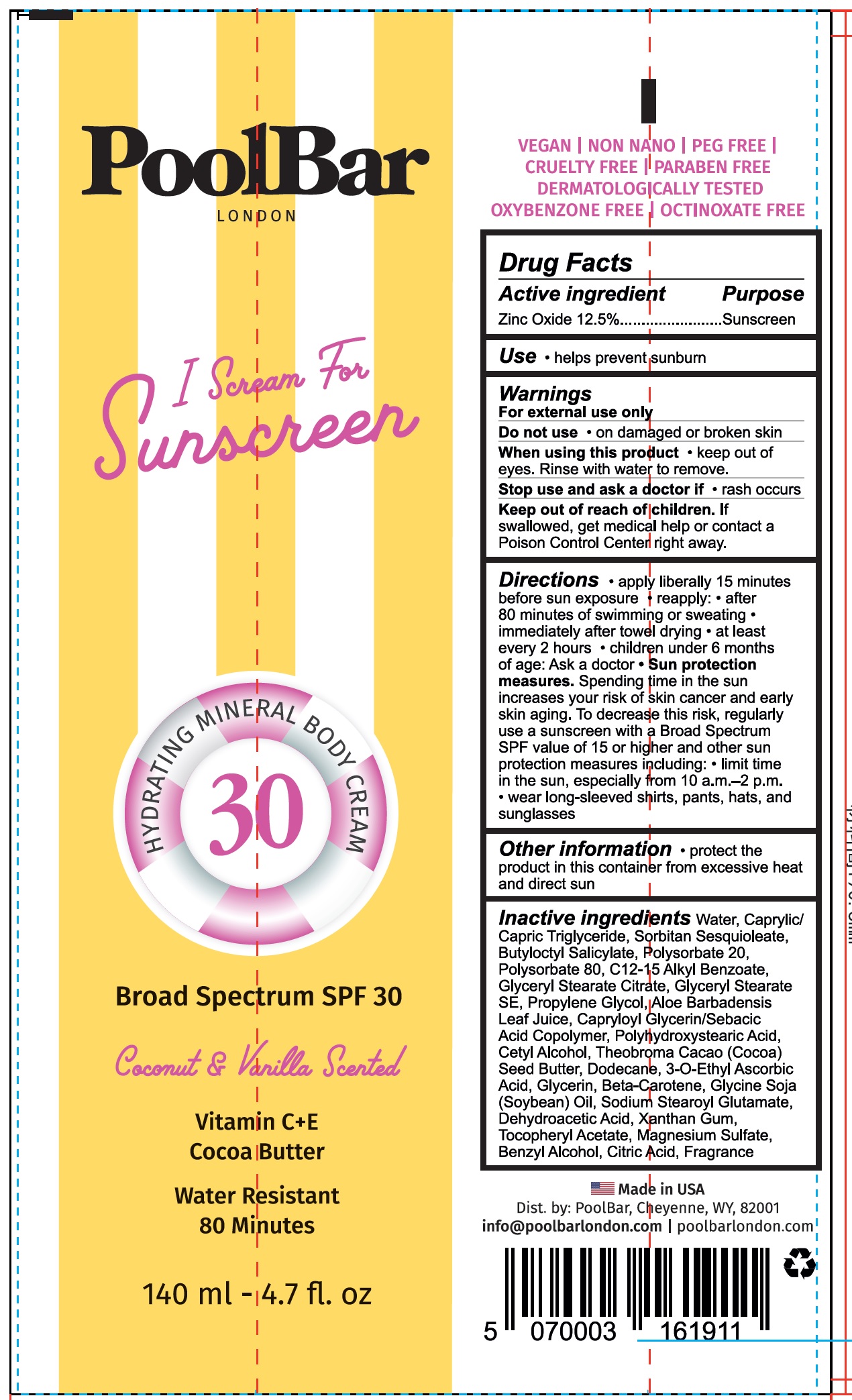 DRUG LABEL: Pool Bar London I Scream For Sunscreen Hydrating Mineral Body Cream SPF 30 Coconut and Vanilla Scented
NDC: 84953-563 | Form: CREAM
Manufacturer: POOLBAR
Category: otc | Type: HUMAN OTC DRUG LABEL
Date: 20241119

ACTIVE INGREDIENTS: ZINC OXIDE 125 mg/1 mL
INACTIVE INGREDIENTS: WATER; CAPRYLIC/CAPRIC TRIGLYCERIDE; SORBITAN SESQUIOLEATE; BUTYLOCTYL SALICYLATE; POLYSORBATE 20; POLYSORBATE 80; C12-15 ALKYL BENZOATE; GLYCERYL STEARATE SE; PROPYLENE GLYCOL; ALOE VERA LEAF; CETYL ALCOHOL; COCOA BUTTER; DODECANE; 3-O-ETHYL ASCORBIC ACID; GLYCERIN; BETA-CAROTENE; SOYBEAN OIL; SODIUM STEAROYL GLUTAMATE; DEHYDROACETIC ACID; XANTHAN GUM; .ALPHA.-TOCOPHEROL ACETATE; MAGNESIUM SULFATE; BENZYL ALCOHOL; CITRIC ACID MONOHYDRATE

Pool Bar London I Scream For Sunscreen Hydrating Mineral Body Cream SPF 30, Coconut & Vanilla Scented

Active ingredient

Zinc Oxide 12.5%

Purpose

Sunscreen

Use

- helps prevent sunburn

Warnings

For external use only

Do not use

- on damaged or broken skin

When using this product

- keep out of eyes. Rinse with water to remove.

Stop use and ask a doctor if

- rash occurs

Keep out of reach of children.

If swallowed, get medical help or contact a Poison Control Center right away.

Directions

- apply liberally 15 minutes before sun exposure
- reapply:
- after 80 minutes of swimming or sweating
- immediately after towel drying
- at least every 2 hours
- children under 6 months of age: Ask a doctor
- Sun protection measures.Spending time in the sun increases your risk of skin cancer and early skin aging. To decrease the risk, regularly use a sunscreen with a Broad Spectrum SPF of 15 or higher and other sun protection measures including:limit time in the sun, especially from 10 a.m. - 2 p.m.
- wear long-sleeved shirts, pants, hats, and sunglasses

Other information

- protect the product in this container from excessive heat and direct sun

Inactive ingredients

Water, Caprylic/Capric Triglyceride, Sorbitan Sesquioleate, Butyloctyl Salicylate, Polysorbate 20, Polysorbate 80, C12-15 Alkyl Benzoate, Glyceryl Stearate SE, Propylene Glycol, Aloe Barbadensis Leaf Juice, Capryloyl Glycerin/Sebacic Acid Copolymer, Polyhydroxystearic Acid, Cetyl Alcohol, Theobroma Cacao (Cocoa) Seed Butter, Dodecane, 3-O-Ethyl Ascorbic Acid, Glycerin, Beta-Carotene, Glycine Soja (Soyabean) Oil, Sodium Stearoyl Glutamate, Dehydroacetic Acid, Xanthan Gum, Tococpheryl Acetate, Magnesium Sulfate, Benzyl Alcohol, Citric Acid, Fragrance